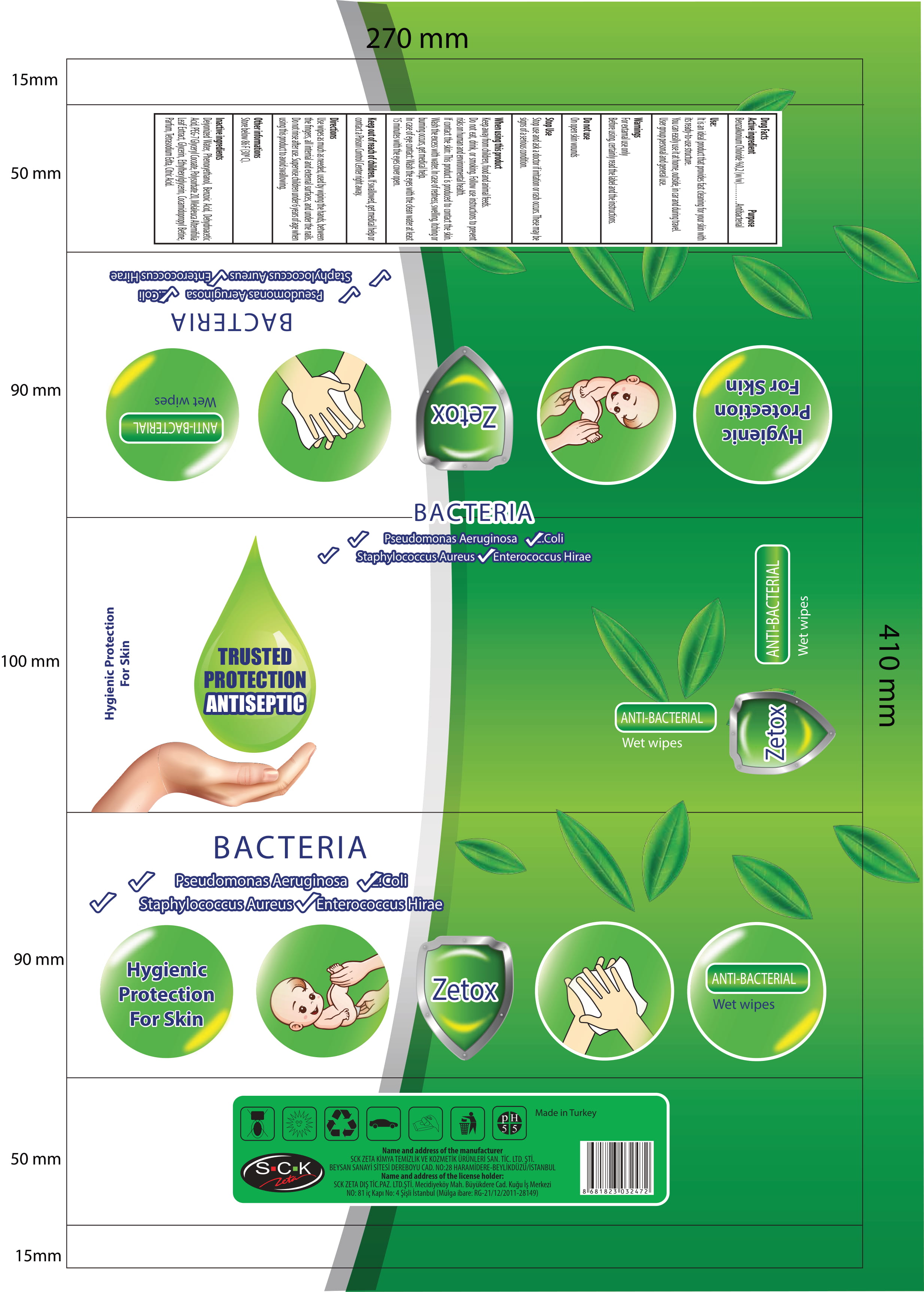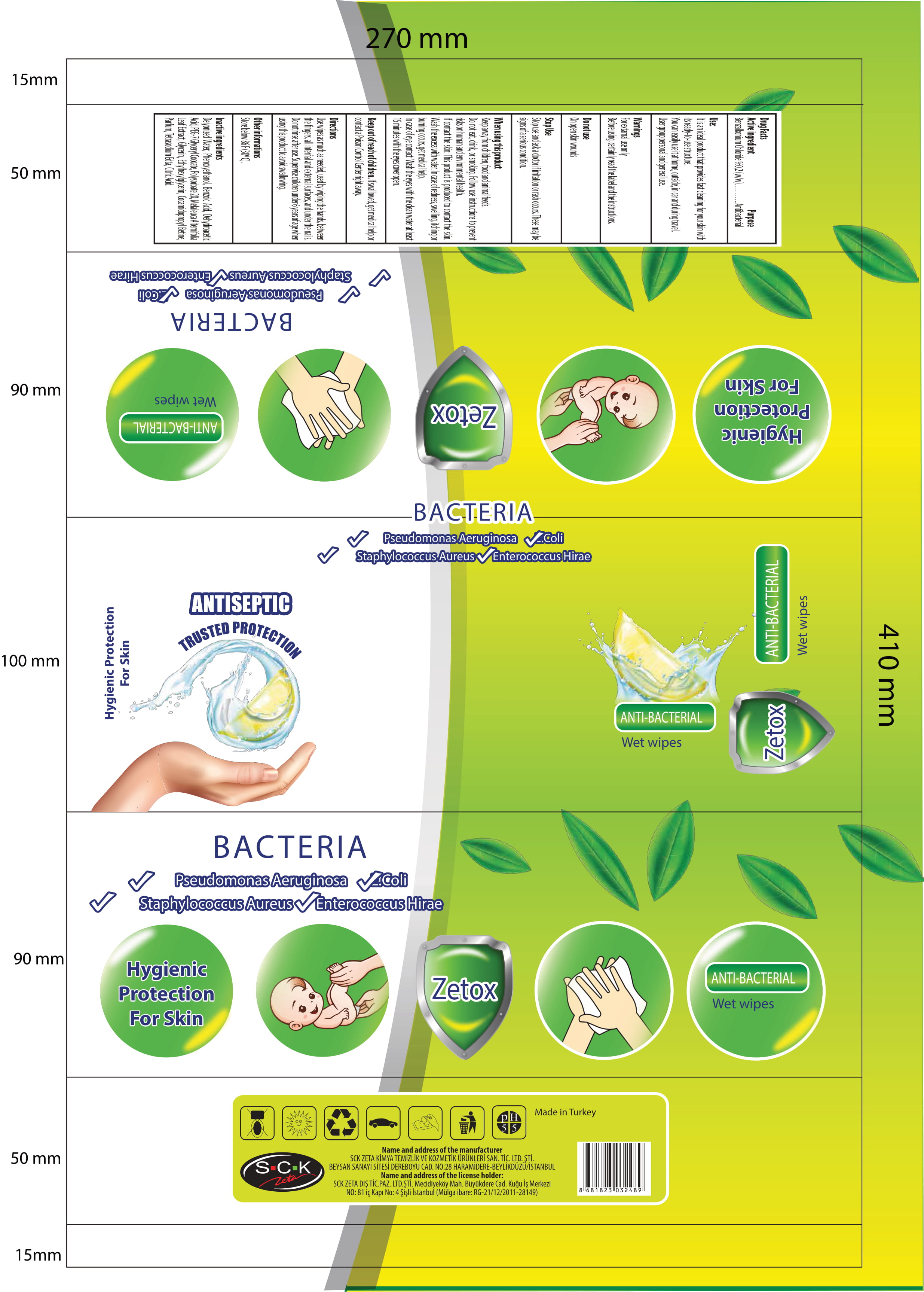 DRUG LABEL: Zetox Antibacterial Wet Wipes
NDC: 86818-004 | Form: CLOTH
Manufacturer: SCK ZETA DIS TICARET
Category: otc | Type: HUMAN OTC DRUG LABEL
Date: 20220123

ACTIVE INGREDIENTS: BENZALKONIUM CHLORIDE 0.2 g/100 g
INACTIVE INGREDIENTS: ANHYDROUS CITRIC ACID; GLYCERIN; PHENOXYETHANOL; WATER; BENZOIC ACID; DEHYDROACETIC ACID; PEG-7 GLYCERYL COCOATE; POLYSORBATE 20; MELALEUCA ALTERNIFOLIA LEAF; ETHYLHEXYLGLYCERIN; COCAMIDOPROPYL BETAINE; ETIDRONATE TETRASODIUM

Zetox Antibacterial Wet Wipes

This is a hand sanitizer manufactured according to the Temporary Policy for Preparation of Certain Hand Sanitizer Products During the Public Health Emergency (CoViD-19); Guidance for Industry.

The hand sanitizer is manufactured using only the following United States Pharmacopoeia (USP) grade ingredients in the preparation of the product (percentage in final product formulation) consistent with World Health Organization (WHO) recommendations:

1. Benzalkonium Chloride 0.2 % (w/w)
2. Glycerin
3. Phenoxyethanol
4. Water
5. Benzoic Acid
6. Etidronate Tetrasodium
7. Peg-7 Glyceryl Cocoate
8. Polysorbate 20
9. Melaleuca Alternifolia Leaf
10. Ethylhexylglycerin
11. Cocamidopropyl Betaine
12. Anhydrous Citric Acid
13. Dehydroacetic Acid The firm does not add other active or inactive ingredients. Different or additional ingredients may impact the quality and potency of the product.

Active Ingredient(s)

Benzalkonium Chloride 0.2% w/w. Purpose: Antibacterial

Purpose

Antiseptic, Antibacterial, Hand Sanitizer

Use

It is an ideal product that provides fast cleaning for your skin with its ready-to-use structure. You can easily use it at home, outside, in car and during travel. User group personal and general use.

Warnings

For external use only.

Before using, certainly read the label and the instructions.

Do not use

- on open skin wounds

When using this product Keep out of reach of children, food and animal feeds. Do not eat, dirnk and smoking. Follow use instructions to prevent risks on human and environmental health.If contact the skin: This product is produced to contact the skin. Wash the excess with water. In case of redness, swelling, itching or burning occurs, get medical help.In case of eye contact: wash the eyes with the clean water at least 15 minutes with the eyes cover open. If swallowed shake the mouth with water. Do not induce vomiting. Immediately apply to the doctor and show him the label of the product.

Stop use and ask a doctor if irritation or rash occurs. These may be signs of a serious condition.

Keep out of reach of children. If swallowed, get medical help or contact a Poison Control Center right away.

Directions

- use wipes as much as needed, used by wiping the hands, between the fingers, all internal and external surfaces, and under the nails. Do not rinse after use.

Other information

Store below 30C (86F

Inactive ingredients

Glycerin, Phenoxyethanol, Water, Benzoic Acid, Tetrasodium EDTA, Peg-7 Glyceryl Cocoate, Polysorbate 20, Melaleuca Alternifolia Leaf Extract, Parfum, Ethylhexylglycerin, Cocamidopropyl Betaine, Citric Acid,Dehydroacetic Acid